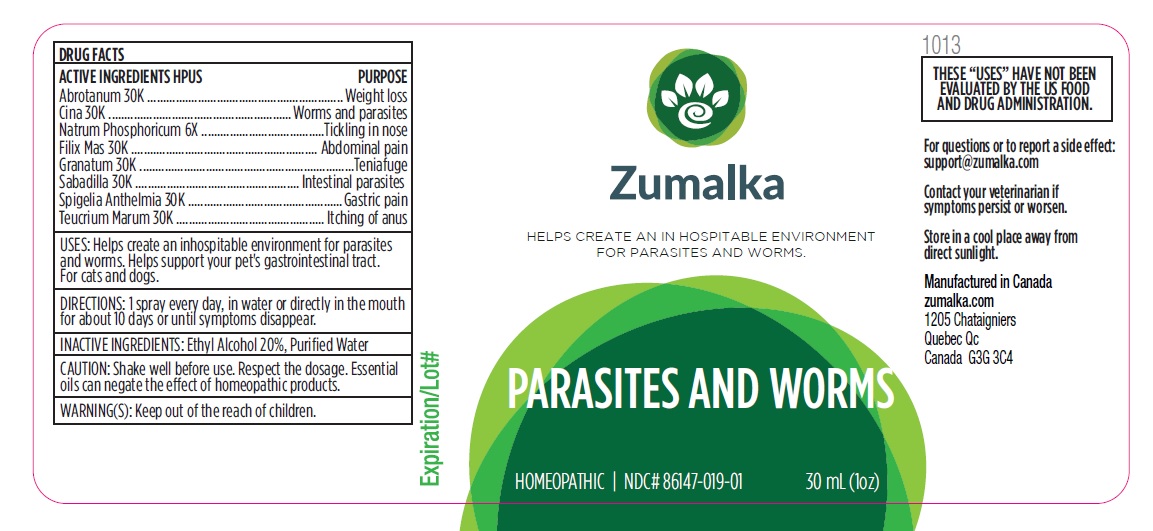 DRUG LABEL: PARASITES AND WORMS
NDC: 86147-019 | Form: LIQUID
Manufacturer: Groupe Cyrenne Inc.
Category: homeopathic | Type: OTC ANIMAL DRUG LABEL
Date: 20251120

ACTIVE INGREDIENTS: ARTEMISIA ABROTANUM FLOWERING TOP 30 [kp_C]/30 mL; ARTEMISIA CINA PRE-FLOWERING TOP 30 [kp_C]/30 mL; DRYOPTERIS FILIX-MAS ROOT 30 [kp_C]/30 mL; PUNICA GRANATUM ROOT BARK 30 [kp_C]/30 mL; SODIUM PHOSPHATE, DIBASIC, HEPTAHYDRATE 30 [kp_C]/30 mL; SCHOENOCAULON OFFICINALE SEED 30 [kp_C]/30 mL; SPIGELIA MARILANDICA ROOT 30 [kp_C]/30 mL; TEUCRIUM MARUM WHOLE 30 [kp_C]/30 mL
INACTIVE INGREDIENTS: WATER; ALCOHOL

Active ingredient Purpose

Abrotanum 30k Weight loss

Cina 30k Worms and parasites

Filix Mas 30k Abdominal pain

Granatum 30k Teniafuge

Natrum Phosphoricum 6x Tickling in nose

Sabadilla 30k Intestinal parasites

Spigelia Anthelmia 30k Gastric pain

Teucrium Marum 30k Itching of anus

Uses

Helps create an inhospitable environment for parasites and worms. Helps support your pet's gastrointestinal tract. For cats and dogs.

Warnings

Keep out of reach of children.

Direction

1 spray every day, in water or directly in the mouth for about 10 days or until symptoms disappear.

Inactive ingredient

Ethyl alcohol 20%, purified water

Cautions

Shake well before use. Respect the dosage. Essential oils can negate the effects of homeopathic products. Store in a cool place away from direct sunlight.